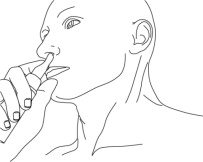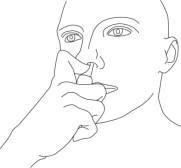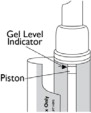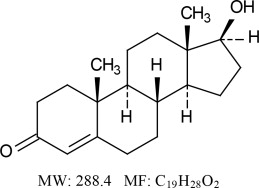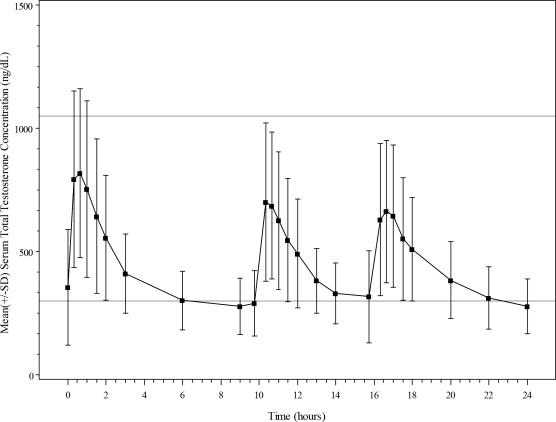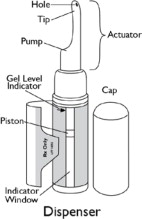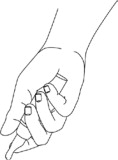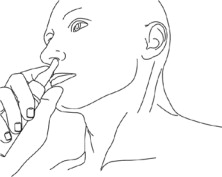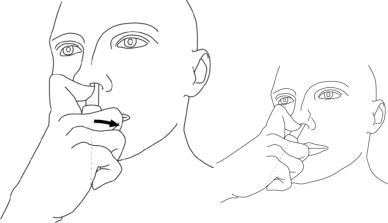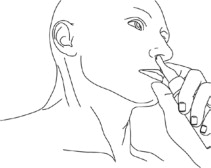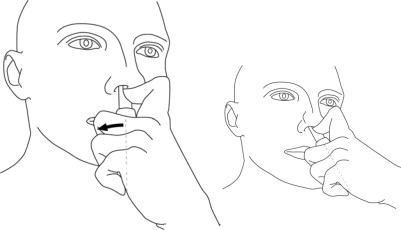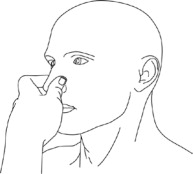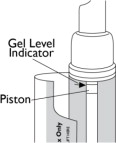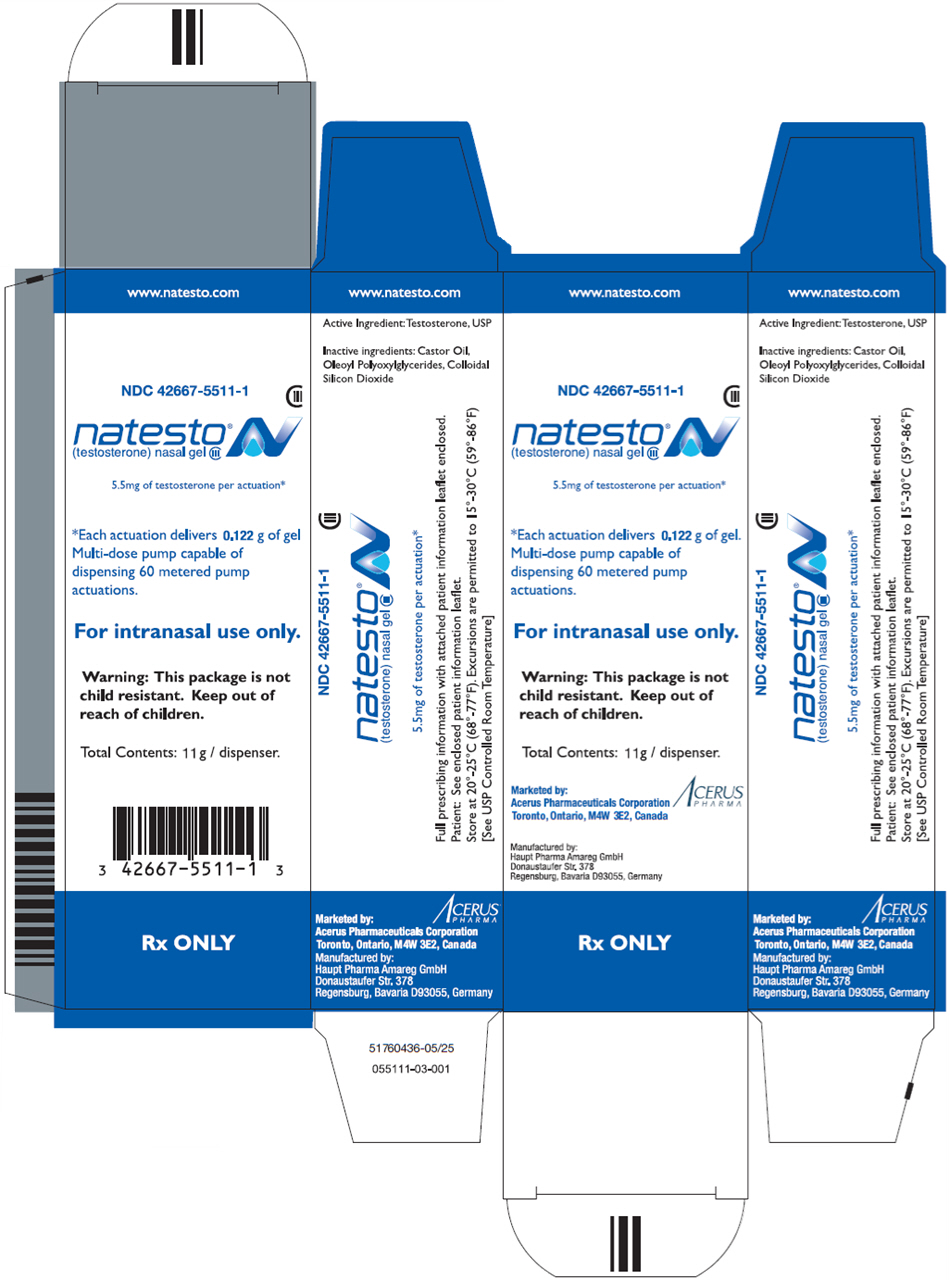 DRUG LABEL: Natesto

NDC: 42667-5511 | Form: GEL, METERED
Manufacturer: Acerus Pharmaceuticals Corporation
Category: prescription | Type: HUMAN PRESCRIPTION DRUG LABEL
Date: 20250724
DEA Schedule: CIII

ACTIVE INGREDIENTS: TESTOSTERONE 5.5 mg/0.122 g
INACTIVE INGREDIENTS: CASTOR OIL; APRICOT KERNEL OIL; SILICON DIOXIDE

HIGHLIGHTS OF PRESCRIBING INFORMATION

These highlights do not include all the information needed to use NATESTO safely and effectively. See full prescribing information for NATESTO.
Natesto (testosterone) nasal gel CIII Initial U.S. Approval: 1953

RECENT MAJOR CHANGES

Warnings and Precautions, Venous Thromboembolism (5.4) | 07/2025
Warnings and Precautions, Blood Pressure Increases (5.6) | 07/2025
Warnings and Precautions, Cardiovascular Risk (5.6) | Removed 07/2025

1. INDICATIONS AND USAGE

Natesto is an androgen indicated for replacement therapy in males for conditions associated with a deficiency or absence of endogenous testosterone:

- Primary hypogonadism (congenital or acquired) (1)
- Hypogonadotropic hypogonadism (congenital or acquired) (1)

Limitations of use:

- Safety and efficacy of Natesto in men with "age-related hypogonadism" have not been established (1).
- Safety and efficacy of Natesto in males less than 18 years old have not been established. (1, 8.4)

2. DOSAGE AND ADMINISTRATION

- Prior to initiating Natesto, confirm the diagnosis of hypogonadism by ensuring that serum testosterone has been measured in the morning on at least two separate days and that these concentrations are below the normal range (2).
- The recommended dose of Natesto is 11 mg of testosterone (2 pump actuations, one per nostril), applied intranasally three times daily. (2.1)
- Serum total testosterone concentrations should be checked periodically, starting as soon as one month after initiating treatment with Natesto. If total testosterone concentrations consistently exceed 1050 ng/dL, therapy with Natesto should be discontinued. If total testosterone concentrations are consistently below 300 ng/dL, an alternative treatment should be considered. (2.1)
- Not recommended for use with nasally administered drugs other than sympathomimetic decongestants (e.g., oxymetazoline). (2.3, 7.4, 12.3).

3. DOSAGE FORMS AND STRENGTHS

Natesto nasal gel is available as a metered-dose pump. One pump actuation delivers 5.5 mg of testosterone. (3)

4. CONTRAINDICATIONS

- Men with carcinoma of the breast or known or suspected prostate cancer (4, 5.5)
- Pregnant or breast-feeding women. Testosterone may cause fetal harm (4, 8.1)

5. WARNINGS AND PRECAUTIONS

- Nasal Adverse Reactions and Limited Long-Term Information on Nasal Safety: Instruct patients to report any nasal symptoms or signs (5.1)
- Not recommended for use in patients with chronic nasal conditions or alterations in nasal anatomy. (5.2)
- Venous Thromboembolism: VTE, including deep vein thrombosis (DVT) and pulmonary embolism (PE) have been reported in patients using testosterone products. Evaluate patients with signs or symptoms consistent with DVT or PE. (5.4)
- Worsening of Benign Prostatic Hyperplasia (BPH) and Potential Risk of Prostate Cancer: Monitor patients with benign prostatic hyperplasia (BPH) for worsening of signs and symptoms of BPH. (5.5)
- Blood Pressure Increases: Testosterone can increase blood pressure, which can increase cardiovascular risk over time. Measure blood pressure periodically. Not recommended for use in men with uncontrolled hypertension (5.6)
- Abuse of Testosterone: Testosterone has been subject to abuse, typically at doses higher than recommended for the approved indication and in combination with other anabolic androgenic steroids. (5.7)
- Potential for Adverse Effects on Spermatogenesis: Exogenous administration of androgens may lead to azoospermia (5.9)
- Edema: Edema with or without congestive heart failure (CHF) may be a complication in patients with preexisting cardiac, renal, or hepatic disease. (5.11)
- Sleep apnea: Sleep apnea may occur in those with risk factors. (5.13)
- Monitor prostate-specific antigen (PSA), hematocrit and lipid concentrations periodically. (5.5, 5.3, 5.14)

6. ADVERSE REACTIONS

Most common adverse reactions (incidence ≥3%) are: PSA increased, headache, rhinorrhea, epistaxis, nasal discomfort, nasopharyngitis, bronchitis, upper respiratory tract infection, sinusitis, and nasal scab. (6.1)

To report SUSPECTED ADVERSE REACTIONS, contact Acerus Pharmaceuticals Corporation at 1-833-698-3786 or FDA at 1-800-FDA-1088 or www.fda.gov/medwatch.

7. DRUG INTERACTIONS

- Androgens may decrease blood glucose and therefore may decrease insulin requirements in diabetic patients. (7.1)
- Changes in anticoagulant activity may be seen with androgens. More frequent monitoring of International Normalized Ratio (INR) and prothrombin time is recommended in patients taking warfarin. (7.2)
- Use of testosterone with corticosteroids may result in increased fluid retention. Use with caution, particularly in patients with cardiac, renal, or hepatic disease. (7.3)

8. USE IN SPECIFIC POPULATIONS

There are insufficient long-term safety data in geriatric patients using Natesto to assess the potential risks of cardiovascular disease and prostate cancer. (8.5)

FULL PRESCRIBING INFORMATION

1. INDICATIONS AND USAGE

Natesto is indicated for replacement therapy in adult males for conditions associated with a deficiency or absence of endogenous testosterone.

- Primary hypogonadism (congenital or acquired): testicular failure due to conditions such as cryptorchidism, bilateral torsion, orchitis, vanishing testis syndrome, orchiectomy, Klinefelter's syndrome, chemotherapy, or toxic damage from alcohol or heavy metals. These men usually have low serum testosterone concentrations and gonadotropins (follicle-stimulating hormone [FSH], luteinizing hormone [LH]) above the normal range.
- Hypogonadotropic hypogonadism (congenital or acquired): gonadotropin or luteinizing hormone-releasing hormone (LHRH) deficiency or pituitary-hypothalamic injury from tumors, trauma, or radiation. These men have low testosterone serum concentrations but have gonadotropins in the normal or low range.

Limitations of use:

- Safety and efficacy of Natesto in men with "age-related hypogonadism" (also referred to as "late-onset hypogonadism") have not been established.
- Safety and efficacy of Natesto in males less than 18 years old have not been established [see Use in Specific Populations (8.4)].

2. DOSAGE AND ADMINISTRATION

Prior to initiating Natesto, confirm the diagnosis of hypogonadism by ensuring that serum testosterone concentrations have been measured in the morning on at least two separate days and that these serum testosterone concentrations are below the normal range.

2.1. Dosing

The recommended dose of Natesto is 11 mg of testosterone (2 pump actuations; 1 actuation per nostril) administered intranasally three times daily for a total daily dose of 33 mg.

Serum total testosterone concentrations should be checked periodically, starting as soon as one month after initiating treatment with Natesto. When the total testosterone concentration consistently exceeds 1050 ng/dL, therapy with Natesto should be discontinued. If the total testosterone concentration is consistently below 300 ng/dL, an alternative treatment should be considered.

2.2. Administration Instructions

Natesto is administered intranasally three times daily once in the morning, once in the afternoon and once in the evening (6 to 8 hours apart), preferably at the same time each day. Patients should be instructed to completely depress the pump 1 time in each nostril to receive the total dose. Do not administer Natesto to other parts of the body.

Preparing the Pump

When using Natesto for the first time, patients should be instructed to prime the pump by inverting the pump, depressing the pump 10 times, and discarding any small amount of product dispensed directly into a sink and then washing the gel away thoroughly with warm water. The tip should be wiped with a clean, dry tissue. If the patient gets Natesto gel on their hands, it is recommended that they wash their hands with warm water and soap. This priming should be done only prior to the first use of each dispenser.

Administering the Dose

To administer the dose, patients should be instructed to perform the following steps:

- Blow the nose.
- Remove the cap from the dispenser.
- Place the right index finger on the pump of the actuator and while in front of a mirror, slowly advance the tip of the actuator into the left nostril upwards until their finger on the pump reaches the base of the nose.
- Tilt the actuator so that the opening on the tip of the actuator is in contact with the lateral wall of the nostril to ensure that the gel is applied to the nasal wall.
- Slowly and firmly depress the pump until it fully stops.
- Remove the actuator from the nose while wiping the tip along the inside of the lateral nostril wall to fully transfer the gel.
- Using your left index finger, repeat the steps outlined in bullets 3 through 6 for the right nostril.
- Use a clean, dry tissue to wipe the tip of the actuator.
- Replace the cap on the dispenser.
- Press on the nostrils at a point just below the bridge of the nose and lightly massage.
- Refrain from blowing the nose or sniffing for 1 hour after administration.

The dispenser should be replaced when the top of the piston inside the dispenser reaches the arrow at the top of the inside label. The inside label may be found by unwrapping the outer flap from around the container.

2.3. Use with Nasally Administered Drugs Other Than Sympathomimetic Decongestants

The drug interaction potential between Natesto and nasally administered drugs other than sympathomimetic decongestants is unknown. Therefore, Natesto is not recommended for use with nasally administered drugs other than sympathomimetic decongestants

(e.g., oxymetazoline) [see Drug Interactions (7.4) and Clinical Pharmacology (12.3)].

2.4. Temporary Discontinuation of Use for Severe Rhinitis

If the patient experiences an episode of severe rhinitis, temporarily discontinue Natesto therapy pending resolution of the severe rhinitis symptoms. If the severe rhinitis symptoms persist, an alternative testosterone replacement therapy is recommended.

3. DOSAGE FORMS AND STRENGTHS

Natesto is a slightly yellow gel for intranasal use and is available in a dispenser with a metered dose pump. One pump actuation delivers 5.5 mg of testosterone.

4. CONTRAINDICATIONS

Natesto is contraindicated in men with carcinoma of the breast or known or suspected carcinoma of the prostate [ see Warnings and Precaution (5.5)].

Natesto is contraindicated in women who are or who may become pregnant, or who are breast- feeding. Natesto may cause fetal harm when administered to a pregnant woman. Natesto may cause serious adverse reactions in nursing infants. Exposure of a fetus or nursing infant to androgens may result in varying degrees of virilization. If a pregnant woman is exposed to Natesto, she should be apprised of the potential hazard to the fetus [ see Warnings and Precautions (5.8) and Use in Specific Populations (8.1, 8.3)].

5. WARNINGS AND PRECAUTIONS

5.1 Nasal Adverse Reactions and Limited Long-Term Information on Nasal Safety

Nasal adverse reactions, including nasopharyngitis, rhinorrhea, epistaxis, nasal discomfort and nasal scabbing, were reported in the clinical trial experience with Natesto. All nasal adverse reactions except one (a single case of upper respiratory infection) were reported as mild or moderate in severity; however, long-term clinical trial data on nasal safety is available in a limited number of subjects [ see Adverse Reactions (6.2)]. Patients should be instructed to report any nasal symptoms or signs to their health care professional. In that circumstance, health care professionals should determine whether further evaluation (e.g., otorhinolaryngology consultation) or discontinuation of Natesto is appropriate.

5.2 Use in Patients with Chronic Nasal Conditions and Alterations in Nasal Anatomy

Due to lack of clinical data on the safety or efficacy, Natesto is not recommended for use in the following patients:

- History of nasal disorders;
- History of nasal or sinus surgery;
- History of nasal fracture within the previous 6 months or nasal fracture that caused a deviated anterior nasal septum;
- Mucosal inflammatory disorders (e.g, Sjogren's syndrome); and
- Sinus disease.

5.3 Polycythemia

Increases in hematocrit, reflective of increases in red blood cell mass, may require discontinuation of Natesto. Check hematocrit prior to initiating testosterone treatment. It would be appropriate to re-evaluate the hematocrit 3 to 6 months after starting testosterone treatment, and then annually. If hematocrit becomes elevated, stop therapy until hematocrit decreases to an acceptable level. An increase in red blood cell mass may increase the risk of thromboembolic events.

5.4 Venous Thromboembolism

There have been postmarketing reports of venous thromboembolic events, including deep vein thrombosis (DVT) and pulmonary embolism (PE), in patients using testosterone products such as Natesto.

In the Testosterone Replacement therapy for Assessment of long-term Vascular Events and efficacy ResponSE in hypogonadal men (TRAVERSE) Study, a randomized, double-blind, placebo-controlled, cardiovascular (CV) outcomes study, compared to placebo, topical testosterone gel was associated with a numerically higher incidence of VTE (1.7% vs 1.2%) which included DVT (0.6% vs 0.5%) and PE events (0.9% vs 0.5%) [see Adverse Reactions (6.1)] .

Evaluate patients who report symptoms of pain, edema, warmth and erythema in the lower extremity for (DVT) and those who present with acute shortness of breath for PE. If a venous thromboembolic event is suspected, discontinue treatment with Natesto and initiate appropriate workup and management [see Adverse Reactions (6.2)].

5.5 Worsening of Benign Prostatic Hyperplasia and Potential Risk of Prostate Cancer

- Patients with BPH treated with androgens are at an increased risk for worsening of signs and symptoms of BPH. Monitor patients with BPH for worsening signs and symptoms.
- Patients treated with androgens may be at increased risk for prostate cancer. Evaluate patients for prostate cancer prior to initiating treatment. It would be appropriate to re-evaluate patients 3 to 6 months after initiation of treatment and then in accordance with prostate cancer screening practices [see Contraindications (4)].

5.6 Blood Pressure Increases

Testosterone products, such as Natesto, can increase blood pressure. Blood pressure increases can increase cardiovascular (CV) risk over time.

The CV risk associated with topical testosterone gel was evaluated in TRAVERSE, randomized, double-blind, placebo-controlled, CV outcomes study in men with a history of CV disease or multiple CV risk factors. In TRAVERSE, topical testosterone gel increased mean systolic blood pressure by 1.0 mm Hg from baseline to 36 months, whereas a mean decrease from baseline of 0.5 mm Hg was observed in the placebo group at this timepoint, for a mean between-group difference of 1.5 mm Hg. However, the incidences of major adverse cardiovascular events (MACE), including cardiovascular death, non-fatal myocardial infarction [MI] and non-fatal stroke, were similar between treatment groups (7% for topical testosterone gel vs 7.3% for placebo) [See Adverse Reactions (6.1)] .

Monitor blood pressure periodically in men using Natesto, especially men with hypertension. Natesto is not recommended for use in patients with uncontrolled hypertension.

5.7 Abuse of Testosterone and Monitoring of Serum Testosterone Concentrations

Testosterone has been subject to abuse, typically at doses higher than recommended for the approved indication and in combination with other anabolic androgenic steroids. Anabolic androgenic steroid abuse can lead to serious cardiovascular and psychiatric adverse reactions [see Drug Abuse and Dependence (9)].

If testosterone abuse is suspected, check serum testosterone concentrations to ensure they are within therapeutic range. However, testosterone levels may be in the normal or subnormal range in men abusing synthetic testosterone derivatives. Counsel patients concerning the serious adverse reactions associated with abuse of testosterone and anabolic androgenic steroids. Conversely, consider the possibility of testosterone and anabolic androgenic steroid abuse in suspected patients who present with serious cardiovascular or psychiatric adverse events.

5.8 Not for Use in Women

Due to lack of controlled studies in women and potential virilizing effects, Natesto is not indicated for use in women.

5.9 Potential for Adverse Effects on Spermatogenesis

With large doses of exogenous androgens, including Natesto, spermatogenesis may be suppressed through feedback inhibition of pituitary follicle-stimulating hormone (FSH), which could possibly lead to adverse effects on semen parameters, including sperm count.

5.10 Hepatic Adverse Effects

Prolonged use of high doses of orally active 17-alpha-alkyl androgens (methyltestosterone) has been associated with serious hepatic adverse effects (peliosis hepatis, hepatic neoplasms, cholestatic hepatitis, and jaundice). Peliosis hepatis can be a life-threatening or fatal complication. Long-term therapy with intramuscular testosterone enanthate has produced multiple hepatic adenomas. Natesto is not known to cause these adverse effects. Nonetheless, patients should be instructed to report any signs or symptoms of hepatic dysfunction (e.g., jaundice). If these occur, promptly discontinue Natesto while the cause is evaluated.

5.11 Edema

Androgens, including Natesto, may promote retention of sodium and water. Edema, with or without congestive heart failure, may be a serious complication in patients with pre-existing cardiac, renal, or hepatic disease. In addition to discontinuation of the drug, diuretic therapy may be required.

5.12 Gynecomastia

Gynecomastia may develop and may persist in patients being treated with androgens, including Natesto, for hypogonadism .[see Adverse Reactions (6.1)].

5.13 Sleep Apnea

The treatment of hypogonadal men with testosterone may potentiate sleep apnea in some patients, especially those with risk factors such as obesity and chronic lung disease.

5.14 Lipid Changes

Changes in the serum lipid profile may occur. Monitor the lipid profile periodically, particularly after starting testosterone therapy. Changes in serum lipid profile may require discontinuation of testosterone therapy.

5.15 Hypercalcemia

Androgens, including Natesto, should be used with caution in cancer patients at risk of hypercalcemia (and associated hypercalciuria). Regular monitoring of serum calcium concentrations is recommended in these patients.

5.16 Decreased Thyroxine-binding Globulin

Androgens, including Natesto, may decrease concentrations of thyroxine-binding globulins, resulting in decreased total T4 serum concentrations and increased resin uptake of T3 and T4. Free thyroid hormone concentrations remain unchanged; however, and there is no clinical evidence of thyroid dysfunction.

6. ADVERSE REACTIONS

6.1 Clinical Trial Experience

Because clinical trials are conducted under widely varying conditions, adverse reaction rates observed in the clinical trials of a drug cannot be directly compared with rates in the clinical trials of another drug and may not reflect the rates observed in practice.

Natesto was evaluated in a multicenter, open-label, 90-day clinical study. Patients could continue treatment with Natesto in two, open-label extension periods for an additional 90 and 180 days, respectively. A total of 306 hypogonadal men with morning testosterone concentrations ≤ 300 ng/dL received Natesto. Of these, 78 received Natesto at a dose of 11 mg three times daily.

90-Day Clinical Study

Among the 78 patients who received Natesto three times daily in the 90-day clinical study, the most common adverse reactions were: prostate specific antigen (PSA) increased, headache, rhinorrhea, epistaxis, nasal discomfort, nasopharyngitis, upper respiratory tract infection (URI), sinusitis, bronchitis and nasal scab. PSA increased was considered an adverse reaction by meeting one of two pre-specified criteria: (1) increase from baseline serum PSA greater than 1.4 ug/L, or (2) serum PSA greater than 4.0 ug/L.

Table 1shows adverse reactions reported by ≥3% of patients treated with 11 mg three times daily in the 90-day clinical study.

Table 1: Adverse Reactions Reported by ≥3% of Patients Treated with Natesto (11 mg of testosterone) Three Times Daily in the 90-Day Clinical Study
Adverse Reactions | Natesto (11 mg of Testosterone) Three Times Daily (N=78) n (%)
PSA increased | 4 (5.1)
Headache | 3 (3.8)
Rhinorrhea | 3 (3.8)
Epistaxis | 3 (3.8)
Nasal discomfort | 3 (3.8)
Nasopharyngitis | 3 (3.8)
Bronchitis | 3 (3.8)
Upper respiratory tract infection | 3 (3.8)
Sinusitis | 3 (3.8)
Nasal scab | 3 (3.8)

Adverse reactions reported by >2% but <3% of patients in the 90-day clinical study include: blood pressure increased, dysgeusia, nasal dryness, nasal congestion, and cough.

Extension Periods

Among the 78 patients who received Natesto three times daily in the 90-day clinical study, a total of 69 patients received Natesto three times daily in the first 90-day extension period.

Among these 69 patients, the most common adverse reactions were: nasopharyngitis, PSA increased, parosmia, nasal discomfort, rhinorrhea and nasal scab.

Table 2shows adverse reactions reported by ≥3% of patients who received Natesto three times daily in both the 90-day clinical study and in the 90-day extension period.

Table 2: Adverse Reactions Reported by ≥3% of Patients in Both the 90-Day Clinical Study and in the 90-Day Extension Period
Adverse Reactions | Natesto 11 mg TID (N=69) n (%)
Nasopharyngitis | 6 (8.7)
Rhinorrhea | 5 (7.2)
PSA increased | 4 (5.8)
Parosmia | 4 (5.8)
Nasal discomfort | 4 (5.8)
Nasal Scab | 4 (5.8)
Upper respiratory tract infection | 3 (4.3)
Bronchitis | 3 (4.3)
Procedural pain | 3 (4.3)
Pain in extremity | 3 (4.3)
Headache | 3 (4.3)
Epistaxis | 3 (4.3)

A total of 18 patients received Natesto three times daily in all three treatment periods, including the 90-day clinical study, the first 90-day extension period, and the second 180-day extension period. Among these 18 patients, the following adverse reactions were reported in more than one patient each: nasopharyngitis, parosmia, PSA increased, nasal discomfort, nasal scab and hypertension. The following adverse reactions were reported in one patient each: nausea, nasal excoriation, thyroid stimulating hormone increased, decreased appetite, myalgia, anosmia, testicular atrophy, epistaxis, nasal septum disorder, nasal discomfort, and rhinorrhea.

In patients who received Natesto three times daily, mean serum PSA concentrations increased by 0.2 ng/mL, 0.1 ng/mL, and 0.2 ng/mL after 90, 180 and 360 days, respectively.

Discontinuations due to Adverse Reactions

Among all subjects (n=306) who received Natesto at any dose in the 90-day clinical study and its 90- and 180-day extension periods, a total of 6 subjects withdrew from treatment for the following adverse reactions, reported by 1 subject each: nasal discomfort, headache, dysgeusia, PSA increased, allergic reaction (hives, swollen lips and tongue), and 1 patient with myalgia, arthralgia, fever, chills and petechiae.

Increased Hematocrit

Among all subjects (n=306) who received Natesto at any dose in the 90-day clinical study and its 90- and 180-day extension periods, a total of 4 subjects had a hematocrit level > 55%. These 4 patients had baseline hematocrits of 48% and 51%. In no case did hematocrit exceed 58%.

Nasal Adverse Reactions

Among all subjects (n=306) who received Natesto at any dose in the 90-day clinical study and its 90- and 180-day extension periods, the following nasal adverse reactions were reported: nasopharyngitis (8.2%), rhinorrhea (7.8%), epistaxis (6.5%), nasal discomfort (5.9%), parosmia (5.2%), nasal scab (5.2%), upper respiratory infection (4.2%), nasal dryness (4.2%), and nasal congestion (3.9%).

Cardiovascular Outcomes

TRAVERSE was a randomized, double-blind, cardiovascular outcomes study to assess the cardiovascular (CV) safety of topical testosterone gel compared to placebo in 5198 hypogonadal men aged 45 to 80 years with a history of CV disease or with multiple CV risk factors. The primary outcome was the incidence of the composite endpoint of major adverse cardiovascular events (MACE), consisting of CV death, non-fatal myocardial infarction (MI), and non-fatal stroke.

The mean duration of therapy was approximately 22 months. The mean duration of follow-up was 33 months. Approximately 61% of all patients discontinued topical testosterone gel or placebo therapy.

The mean patient age (±SD) was 63.3 (7.9) years with 2452 patients aged 65 years or more (47%); 2847 (about 55%) patients had pre-existing cardiovascular disease, whereas 2357 patients (about 45%) had an elevated cardiovascular risk at baseline, and mean BMI was 35 kg/m^2. Approximately 80% of patients were White, 17% were Black, and 3% were of other races or ethnic groups. Approximately 69%, 84%, and 93% had diabetes mellitus, hyperlipidemia, and hypertension, respectively.

The mean serum testosterone concentration at baseline in patients receiving topical testosterone gel was 220.4 ng/dL (n=2596). The mean serum testosterone concentrations at 12 months, 24 months, 36 months, and 48 months in patients receiving topical testosterone gel were 440.5 ng/dL (n=1683), 420.9 ng/dl (n=1125), 428.7 ng/dL (n=731), and 365.2 ng/dL (n=220), respectively.

For patients treated with topical testosterone gel, the incidence of MACE was 7.0% (n=182 events) and for those receiving placebo, the incidence of MACE was 7.3% (n=190 events). The study demonstrated non-inferiority of topical testosterone gel versus placebo because the upper bound of 95% CI was less than the pre-specified risk margin, of 1.5 for MACE (Hazard Ratio 0.96 [95% CI: 0.78, 1.17]).

Additional Adverse Reactions Reported in TRAVERSE

Additional adverse reactions reported in TRAVERSE at an incidence rate >2% in either treatment group and greater in topical testosterone gel versus placebo included: nonfatal arrythmias warranting intervention (5.2% vs 3.3%), atrial fibrillation (3.5% vs 2.4%), acute kidney injury (2.3% vs 1.5%) and bone fracture (3.5% vs 2.5%). For the adverse reaction of bone fracture, each event was adjudicated by clinical review.

6.2 Postmarketing Experience

The following adverse reactions have been identified during post-approval use of testosterone. Because these reactions are reported voluntarily from a population of uncertain size, it is not always possible to reliably estimate their frequency or establish a causal relationship to drug exposure.

Cardiovascular Disorders: myocardial infarction, stroke [see Warnings and Precautions (5.6)]

Vascular Disorders: Venous thromboembolism [see Warnings and Precautions (5.4)]

7. DRUG INTERACTIONS

7.1 Insulin

Changes in insulin sensitivity or glycemic control may occur in patients treated with androgens. In diabetic patients, the metabolic effects of androgens may decrease blood glucose and, therefore, may necessitate a decrease in the dose of anti-diabetic medication.

7.2 Oral Anticoagulants

Changes in anticoagulant activity may be seen with androgens, therefore more frequent monitoring of international normalized ration (INR) and prothrombin time is recommended in patients taking warfarin, especially at the initiation and termination of androgen therapy.

7.3 Corticosteroids

The concurrent use of testosterone with corticosteroids may result in increased fluid retention and requires monitoring particularly in patients with cardiac, renal, or hepatic disease.

7.4 Oxymetazoline

A 2.6% decrease in mean AUC(0-24) and 3.6% decrease in mean Cmaxof total testosterone was observed in males with symptomatic seasonal rhinitis when treated with oxymetazoline 30 minutes prior to Natesto compared to when left untreated. Oxymetazoline does not impact the absorption of testosterone when concomitantly administered with Natesto [see Clinical Pharmacology (12.3)]. Drug interaction potential with other nasally administered drugs other than oxymetazoline has not been studied.

8. USE IN SPECIFIC POPULATIONS

8.1. Pregnancy

Pregnancy Category X — Natesto is contraindicated during pregnancy or in women who may become pregnant. Testosterone is teratogenic and may cause fetal harm. Exposure of a fetus to androgens may result in varying degrees of virilization. If this drug is used during pregnancy or if the patient becomes pregnant while taking this drug, the patient should be apprised of the potential hazard to a fetus.

8.3. Nursing Mothers

Although it is not known how much testosterone transfers into human milk, Natesto is contraindicated in nursing women because of the potential for serious adverse reactions in nursing infants.

8.4. Pediatric Use

Safety and efficacy of Natesto has not been established in pediatric patients less than 18 years of age. Improper use may result in acceleration of bone age and premature closure of epiphyses.

8.5. Geriatric Use

There have not been sufficient numbers of geriatric patients involved in controlled clinical studies utilizing Natesto to determine whether efficacy in those over 65 years of age differs from younger subjects.

Of the 306 patients enrolled in the Phase 3 clinical trial utilizing Natesto, 60 were 65 years of age or older, and 9 were 75 years of age or older. There are insufficient long-term safety data in geriatric patients to assess the potential for increased risks of cardiovascular disease and prostate cancer.

Geriatric patients treated with androgens may also be at risk for worsening of signs and symptoms of BPH [see Warnings and Precautions (5.5)].

8.6. Renal Impairment

No studies were conducted in patients with renal impairment.

8.7. Hepatic Impairment

No studies were conducted in patients with hepatic impairment.

8.8. Use in Men With Body Mass Index greater than 35 kg/m^2

Safety and efficacy of Natesto in males with body mass index greater than 35 kg/m^2has not been established.

8.9. Allergic Rhinitis

Serum total testosterone concentrations were decreased by 21 to 24% in males with symptomatic allergic rhinitis, whether treated with nasal decongestants such as oxymetazoline, or left untreated [see Clinical Pharmacology (12.3)].

9. DRUG ABUSE AND DEPENDENCE

9.1. Controlled Substance

Natesto contains testosterone, a Schedule III controlled substance in the Controlled Substances Act.

9.2. Abuse

Drug abuse is intentional non-therapeutic use of a drug, even once, for its rewarding psychological and physiological effects. Abuse and misuse of testosterone are seen in male and female adults and adolescents. Testosterone, often in combination with other anabolic androgenic steroids (AAS), and not obtained by prescription through a pharmacy, may be abused by athletes and bodybuilders. There have been reports of misuse by men taking higher doses of legally obtained testosterone than prescribed and continuing testosterone despite adverse events or against medical advice.

Abuse-Related Adverse Reactions

Serious adverse reactions have been reported in individuals who abuse anabolic androgenic steroids and include cardiac arrest, myocardial infarction, hypertrophic cardiomyopathy, congestive heart failure, cerebrovascular accident, hepatotoxicity, and serious psychiatric manifestations, including major depression, mania, paranoia, psychosis, delusions, hallucinations, hostility and aggression.

The following adverse reactions have also been reported in men: transient ischemic attacks, convulsions, hypomania, irritability, dyslipidemias, testicular atrophy, subfertility, and infertility.

The following additional adverse reactions have been reported in women: hirsutism, virilization, deepening of voice, clitoral enlargement, breast atrophy, male-pattern baldness, and menstrual irregularities.

The following adverse reactions have been reported in male and female adolescents: premature closure of bony epiphyses with termination of growth, and precocious puberty.

Because these reactions are reported voluntarily from a population of uncertain size and may include abuse of other agents, it is not always possible to reliably estimate their frequency or establish a causal relationship to drug exposure.

9.3. Dependence

Behaviors Associated with Addiction

Continued abuse of testosterone and other anabolic steroids, leading to addiction is characterized by the following behaviors:

- Taking greater dosages than prescribed
- Continued drug use despite medical and social problems due to drug use
- Spending significant time to obtain the drug when supplies of the drug are interrupted
- Giving a higher priority to drug use than other obligations
- Having difficulty in discontinuing the drug despite desires and attempts to do so
- Experiencing withdrawal symptoms upon abrupt discontinuation of use

Physical dependence is characterized by withdrawal symptoms after abrupt drug discontinuation or a significant dose reduction of a drug. Individuals taking supratherapeutic doses of testosterone may experience withdrawal symptoms lasting for weeks or months which include depressed mood, major depression, fatigue, craving, restlessness, irritability, anorexia, insomnia, decreased libido and hypogonadotropic hypogonadism.

Drug dependence in individuals using approved doses of testosterone for approved indications has not been documented.

10. OVERDOSAGE

No cases of overdose with Natesto have been reported in clinical trials. There is 1 report of acute overdosage by injection of testosterone enanthate: testosterone concentrations of up to 11,400 ng/dL were implicated in a cerebrovascular accident.

Treatment of overdosage would consist of discontinuation of Natesto together with appropriate symptomatic and supportive care.

11. DESCRIPTION

Natesto (testosterone) nasal gel is a slightly yellow gel containing 5.5 mg of testosterone in 122.5 mg of Natesto gel for nasal administration. The active pharmacologic ingredient in Natesto is testosterone, an androgen. Testosterone is a white to practically white crystalline powder chemically described as 17β-Hydroxyandrost-4-en-3-one. The structural formula is:

The inactive ingredients are castor oil, oleoyl polyoxylglycerides, and colloidal silicon dioxide.

12. CLINICAL PHARMACOLOGY

12.1. Mechanism of Action

Endogenous androgens, including testosterone and dihydrotestosterone (DHT), are responsible for the normal growth and development of the male sex organs and for maintenance of secondary sex characteristics. These effects include the growth and maturation of the prostate, seminal vesicles, penis, and scrotum; the development of male hair distribution, such as facial, pubic, chest, and axillary hair; laryngeal enlargement, vocal cord thickening, alterations in body musculature, and fat distribution. Testosterone and DHT are necessary for the normal development of secondary sex characteristics.

Male hypogonadism, a clinical syndrome resulting from insufficient secretion of testosterone, has two main etiologies. Primary hypogonadism is caused by defects of the gonads, such as Klinefelter's syndrome or Leydig cell aplasia, whereas secondary hypogonadism is the failure of the hypothalamus (or pituitary) to produce sufficient gonadotropins (FSH, LH).

12.2. Pharmacodynamics

No specific pharmacodynamic studies were conducted using Natesto.

12.3. Pharmacokinetics

Absorption

Natesto delivers physiologic amounts of testosterone, producing circulating concentrations that approximate normal testosterone concentrations (i.e., 300 to 1,050 ng/dL) seen in healthy men. The maximum concentration for Natesto is achieved within approximately 40 minutes of administration and has a half-life ranging from 10 to 100 minutes.

Figure 1summarizes the pharmacokinetic profiles of total testosterone in patients completing 90 days of Natesto treatment administered as 33 mg of testosterone daily (11 mg three times daily).

Figure 1: Mean Serum Total Testosterone Concentrations on Day 90 Following Natesto Administered As 11 mg of Testosterone Three Times Daily (N=69)

The average daily testosterone concentration produced by Natesto administered as 11 mg of testosterone three times daily on Day 90 was 421 (± 116) ng/dL.

Distribution

Circulating testosterone is primarily bound in the serum to sex hormone-binding globulin (SHBG) and albumin. Approximately 40% of testosterone in plasma is bound to SHBG, 2% remains unbound (free), and the rest is loosely bound to albumin and other proteins.

Metabolism

Testosterone is metabolized to various 17-keto steroids through 2 different pathways. The major active metabolites of testosterone are estradiol and dihydrotestosterone (DHT).

DHT concentrations increased in parallel with testosterone concentrations during Natesto treatment. After 90 days of treatment, the mean DHT/testosterone ratio was 0.09 which was within the normal range.

Excretion

About 90% of a dose of testosterone given intramuscularly is excreted in the urine as glucuronic and sulfuric acid conjugates of testosterone and its metabolites; about 6% of a dose is excreted in the feces, mostly in the unconjugated form. Inactivation of testosterone occurs primarily in the liver.

Drug Interactions

Use in patients with allergic rhinitis and oxymetazoline:The effects of allergic rhinitis and the use of oxymetazoline on the absorption of testosterone were investigated in a 3-way cross-over clinical study. Eighteen males with seasonal allergic rhinitis received 3 doses of 11 mg of testosterone intranasally (testosterone dose of 33 mg/day) while they were in the asymptomatic, symptomatic, and symptomatic but treated (with oxymetazoline) states using an environmental challenge chamber model.

Serum total testosterone concentrations were decreased by 21 to 24% in males with symptomatic allergic rhinitis. A 2.6% decrease in mean AUC(0-24) and 3.6% decrease in mean Cmaxof total testosterone was observed in males with symptomatic seasonal rhinitis when treated with oxymetazoline 30 minutes prior to Natesto compared to when left untreated. Oxymetazoline does not impact the absorption of testosterone when concomitantly administered with Natesto [see Clinical Pharmacology (12.3)]. Drug interaction potential with nasally administered drugs other than oxymetazoline has not been studied.

13. NONCLINICAL TOXICOLOGY

13.1. Carcinogenesis, Mutagenesis, and Impairment of Fertility

Carcinogenicity

Testosterone has been tested by subcutaneous injection and implantation in mice and rats. In mice, the implant induced cervical-uterine tumors, which metastasized in some cases. There is suggestive evidence that injection of testosterone into some strains of female mice increases their susceptibility to hepatoma. Testosterone is also known to increase the number of tumors and decrease the degree of differentiation of chemically induced carcinomas of the liver in rats.

Mutagenesis

Testosterone was negative in the in vitro Ames and in the in vivo mouse micronucleus assays.

Impairment of Fertility

The administration of exogenous testosterone has been reported to suppress spermatogenesis in the rat, dog and non-human primates, which was reversible on cessation of the treatment.

14. CLINICAL STUDIES

14.1. Testosterone Replacement Therapy

Natesto was evaluated for efficacy in a 90-day, open-label, multicenter study of 306 hypogonadal men. Eligible patients were 18 years of age and older (mean age 54 years) and had morning serum total testosterone concentrations less than 300 ng/dL. Patients were Caucasian (89%), African-American (6%), Asian (5%), or of other ethnicities (less than 1%).

Patients were instructed to self-administer Natesto (11 mg of testosterone) intranasally either two or three times daily.

The primary endpoint was the percentage of patients with an average serum total testosterone concentration (Cavg) within the normal range (300 to 1050 ng/dL) on Day 90.

The secondary endpoint was the percentage of patients with a maximum total testosterone concentration (Cmax) above three predetermined limits: greater than 1500 ng/dL, between 1800 and 2500 ng/dL, and greater than 2500 ng/dL.

A total of 78 hypogonadal men received Natesto (11 mg of testosterone) three times daily (33 mg of testosterone daily). Of these, a total of 73 hypogonadal men were included in the statistical evaluation of efficacy (total testosterone pharmacokinetics) on Day 90 based on the intent-to-treat (ITT) population with last observation carried forward (LOCF). Ninety percent (90%) of these 73 patients had a Cavgwithin the normal range (300 to 1050 ng/dL) on Day 90. The percentages of patients with Cavgbelow the normal range (less than 300 ng/dL) and above the normal range (greater than 1050 ng/dL) on Day 90 were 10% and 0%, respectively.

Table 3summarizes the mean (SD) serum total testosterone concentrations on Day 90 in 69 patients who had a full pharmacokinetic sampling profile and were treated with Natesto (11 mg of testosterone) three times daily for 90 days.

Table 3: Mean (SD) Serum Total Testosterone Concentrations on Day 90 Following Administration of Natesto (11 mg of testosterone) Three Times Daily
 | Natesto (11 mg of testosterone) Three Times Daily (N=69)
Cavg(ng/dL) | 421 (116)
Cmax(ng/dL) | 1044 (378)
Cmin(ng/dL) | 215 (74)
Cavg= average concentration; Cmax= maximum concentration; Cmin= minimum concentration.

The percentages of patients with Cmaxgreater than 1500 ng/dL and between 1800 and 2500 ng/dL were 15.9% and 1.4%, respectively. No patient had a Cmaxgreater than 2500 ng/dL.

16. HOW SUPPLIED/STORAGE AND HANDLING

16.1. How Supplied

Natesto (testosterone) nasal gel is available as a metered dose pump containing 11 grams of gel dispensed as 60 metered pump actuations. One pump actuation delivers 5.5 mg of testosterone in 0.122 grams of gel.

16.2. Storage

Keep Natesto out of reach of children.

Store at 20°C to 25°C (68°F to 77°F). Excursions are permitted to 15°C to 30°C (59°F to 86°F). See USP Controlled Room Temperature.

16.3. Handling and Disposal

Used Natesto dispensers should be discarded in household trash in a manner that prevents accidental exposure of children or pets.

17. PATIENT COUNSELING INFORMATION

Advise the patient to read the FDA-approved patient labeling (Patient Information).

Use in Men With Known or Suspected Prostate or Breast Cancer

Men with known or suspected prostate or breast cancer should not use Natesto [see Contraindications (4) and Warnings and Precaution (5.5)].

Nasal Adverse Reactions

Nasal adverse reactions, including nasopharyngitis, rhinorrhea, epistaxis, nasal discomfort and nasal scabbing, were reported in clinical trials of Natesto. Advise patients to report any nasal symptoms or signs to their health care professional.

Potential Adverse Reactions With Androgens

Patients should be informed that treatment with androgens may lead to adverse reactions which include:

- Changes in urinary habits such as increased urination at night, trouble starting your urine stream, passing urine many times during the day, having an urge that you have to go to the bathroom right away, having urine accident, being unable to pass urine, and having a weak urine flow.
- Breathing disturbances, including those associated with sleep, or excessive daytime sleepiness.
- Too frequent or persistent erections of the penis.
- Nausea, vomiting, changes in skin color, or ankle swelling.
- Venous thromboembolism, the signs and symptoms of which may include lower limb pain, edema, or erythema; dyspnea; or chest pain.
- Increased blood pressure that can increase cardiovascular risk over time

Patients Should be Advised of the Following Instructions For Use

- Read the Patient Information accompanying each Natesto metered dose pump.
- Prime the pump by depressing it 10 times prior to its first use. No priming is needed with subsequent uses of that pump.
- Administer Natesto intranasally and NOT to other parts of the body. Administer Natesto intranasally three times daily, once in the morning, once in the afternoon and once in the evening (6 to 8 hours apart), preferably at the same time each day.
- Keep Natesto out of the reach of children.
- Report any changes in their state of health, such as signs and symptoms of venous thromboembolism, changes in urinary habits, breathing, sleep, mood, nasal irritation or rhinitis.
- Be aware of the importance of monitoring BP periodically while on Natesto. If BP increases while on Natesto, antihypertensive medications may need to be started, added, or adjusted, or Natesto may need to be discontinued.
- Never share Natesto with anyone.

Acerus Pharmaceuticals Corporation,
Toronto, ON M4W 3E2, Canada

Patient Information
Natesto (Na-tes-to) CIII
(testosterone) nasal gel

What is Natesto?

- Natesto is a prescription medicine that contains testosterone and is used to treat adult males who have low or no testosterone due to certain medical conditions.
- Your healthcare provider will test the testosterone level in your blood before you start and while you are using Natesto.
- It is not known if Natesto is safe or effective to treat men who have low testosterone due to aging.
- It is not known if Natesto is safe or effective in children less than 18 years old. Improper use of Natesto may affect bone growth in children.
- Natesto is a controlled substance (CIII) because it contains testosterone that can be a target for people who abuse prescription medicines. Keep your Natesto in a safe place to protect it. Never give your Natesto to anyone else, even if they have the same symptoms you have. Selling or giving away this medicine may harm others and is against the law.
- Natesto is not meant for use in women.

Who should not use Natesto?
Do not use Natesto if you:

- are a man who has breast cancer
- have or might have prostate cancer
- are pregnant or may become pregnant or are breastfeeding. Natesto may harm your unborn or breastfeeding baby.

Talk to your healthcare provider before using Natesto if you have any of the above conditions.

Before using Natesto, tell your healthcare provider about all of your medical conditions, including if you:

- have or have had nose (nasal) or sinus problems ornasal or sinus surgery
- have had a broken nose (fracture) within the past 6 months
- have or have had a fracture of your nose that caused the inside of your nose to be crooked (deviated anterior nasal septum)
- have or have had problems with swelling of the lining of your nose (mucosal inflammatory disorder)
- have breast cancer
- have or might have prostate cancer
- have urinary problems due to an enlarged prostate
- have high blood pressure or are being treated for high blood pressure
- have heart problems
- have liver or kidney problems
- have problems breathing while you sleep (sleep apnea)

Tell your healthcare provider about all the medicines you take, including prescription and over-the-counter medicines, vitamins, or herbal supplements.
Using Natesto with certain other medicines can affect each other. Especially tell your healthcare provider if you take:

- insulin

- medicines that decrease blood clotting

- corticosteroids

How should I use Natesto?

- See the detailed Instructions for Useat the end of this Patient Information for Instructions about the right way to use Natesto.
- Use Natesto exactly as your healthcare provider tells you to. Your healthcare provider will tell you how much Natesto to use and when to use it.
- Natesto is for use in your nose (intranasally) only.
- Natesto can be used with a type of nasal spray called sympathomimetic decongestants such as oxymetazoline. Natesto should not be used with other nasal sprays. It is not known if Natesto is safe and effective when used with other nasal sprays.

What are the possible side effects of Natesto? Natesto may cause serious side effects, including:

- Nose (nasal) problems.Signs and symptoms of nasal problems may include runny nose, congestion, sneezing, nose bleed, nasal discomfort, nasal scabbing, or nasal dryness.
- If you already have enlargement of your prostate gland, your signs and symptoms can get worse while using Natesto.This can include: Increased urination at night, trouble starting your urine stream, having to pass urine many times during the day, having an urge that you have to go to the bathroom right away, having a urine accident, being unable to pass urine or weak urine flow.
- Possible increased risk of prostate cancer.Your healthcare provider should check you for prostate cancer or any other prostate problems before you start and while you use Natesto.
- Changes in red blood cells.
- Blood clots in your legs or lungs.Signs and symptoms of a blood clot in your legs can include leg pain, swelling or redness. Signs and symptoms of a blood clot in your lungs can include difficulty breathing or chest pain.
- Increased blood pressure. Natesto can increase your blood pressure, which can increase your risk of having a heart attack or stroke over time. Your risk may be greater if you have already had a heart attack or stroke or if you have other risk factors for heart attack or stroke. You may need to start new medicines or have medicines changed for high blood pressure while on Natesto. If your blood pressure cannot be controlled, Natesto may need to be stopped. Your healthcare provider should check your blood pressure while you use Natesto.
- In large doses, Natesto may lower your sperm count.
- Possible increased risk of liver problems.Signs and symptoms of liver problems may include: Nausea or vomiting, yellowing of your skin or whites of your eyes, dark urine, or pain on the right side of your stomach area (abdominal pain).
- Swelling of your ankles, feet, or body, with or without heart failure.This may cause serious problems for people who have heart, kidney, or liver disease.
- Enlarged or painful breasts.
- Problems breathing while you sleep (sleep apnea).

Call your healthcare provider right away if you have any of the serious side effects listed above. These are not all the possible side effects of Natesto. Call your doctor for medical advice about side effects. You may report side effects to FDA at 1-800-FDA-1088.
The most common side effects of Natesto include:

- increased prostate specific antigen (a test used to screen for prostate cancer)
- headache
- runny nose
- nose bleeds
- nose pain
- sore throat
- cough
- upper respiratory infection
- sinus infection
- nose scabs

Other side effects includemore erections than normal for you or erections that last a long time.

How should I store Natesto?

- Store Natesto between 68ºF to 77ºF (20ºC to 25ºC).
- Keep Natesto and all medicines out of the reach of children.

General information about the safe and effective use of Natesto.

Medicines are sometimes prescribed for purposes other than those listed in a Patient Information leaflet. Do not use Natesto for a condition for which it was not prescribed. Do not give Natesto to other people, even if they have the same symptoms that you have. It may harm them.
If you would like more information about Natesto, talk with your healthcare provider. You can ask your pharmacist or healthcare provider for information about Natesto that is written for health professionals. For more information go to www.natesto.comor call 1-833-698-3786.

What are the ingredients in Natesto?
Active ingredient:testosterone
Inactive ingredients:castor oil, oleoyl polyoxylglycerides, and colloidal silicon dioxide
Marketed by: Acerus Pharmaceuticals Corporation, Toronto, ON M4W 3E2, Canada
Manufactured by: Haupt Pharma Amareg GmbH, Donaustaufer Str. 378, Regensburg, Bavaria D-93055, Germany

Instructions for Use
Natesto (Na-tes-to)
CIII (testosterone)
nasal gel

Supplies needed to give your Natesto dose:

- 1 Natesto dispenser
- 2 clean, dry tissues
- a clean and flat surface, like a table
- a mirror

Parts of your Natesto dispenser (See Figure A)

(Figure A)

Information about your Natesto:

- Do notblow your nose or sniff for 1 hour after using Natesto.
- Before you use Natesto for the first time, you will need to prime your Natesto pump.

How to prime your Natesto pump:

- Hold your Natesto dispenser over a sink, turn it upside down (invert) and slowly press the pump and release 10 times (See Figure B).

(Figure B)

- All the Natesto that comes out when you prime your pump should be rinsed down the sink with warm water.
- If there is any Natesto on the tip of your Natesto actuator after priming, wipe the tip with a clean, dry tissue.
- If any Natesto gel gets on your hands, it is recommended to wash your hands with warm water and soap.

Giving your Natesto dose:

Step 1:Blow your nose.

Step 2:Remove the Natesto cap.

Step 3:While looking in the mirror, put your right first (index) finger on the pump of your Natesto actuator and slowly slide the tip of the actuator up into your left nostril until your finger on the pump touches the bottom of your nose (See Figure C).

(Figure C)

Step 4:Gently tilt the Natesto actuator so that the hole in the tip touches the lateral (side) wall of your nostril. This will make sure that Natesto is given in the correct place (See Figure D).

(Figure D)

Step 5:With the actuator in place, slowly and firmly push the pump down until it fully stops and remove the actuator from your nose.

Step 6:While looking in the mirror, put your left first (index) finger on the pump of your Natesto actuator and slowly slide the tip of the actuator up into your right nostril until your finger on the pump touches the bottom of your nose (See Figure E).

(Figure E)

Step 7:Gently tilt the tip of the Natesto actuator so that the hole in the tip touches the lateral (side) wall of your nostril. This will make sure that Natesto is given in the correct place (See Figure F).

(Figure F)

Step 8:Slowly and firmly push down on the pump until it fully stops and remove the actuator from your nose.

Step 9:Wipe the tip of the actuator with a clean, dry tissue.

Step 10:Replace the cap.

Step 11:Press your nostrils together just below the middle of your nose (bridge) and lightly rub them together (See Figure G).

(Figure G)

- Replace your Natesto dispenser when the top of the piston inside the dispenser reaches the arrow at the top of the inside label (See Figure H).

(Figure H)

How to throw away your empty Natesto dispenser:

- Safely throw away your empty Natesto dispenser in your household trash.
- Keep Natesto and all medicines out of the reach of children and pets.

This Patient Information and Instructions for Use have been approved by the U.S. Food and Drug Administration.

Marketed by: Acerus Pharmaceuticals Corporation, Toronto, ON M4W 3E2, Canada

Manufactured by: Haupt Pharma Amareg GmbH, Donaustaufer Str. 378, Regensburg, Bavaria D-93055, Germany

Revised: 12/2021

PRINCIPAL DISPLAY PANEL - 11 g Dispenser Box

www.natesto.com

NDC 42667-5511-1
CIII

natesto®
(testosterone) nasal gel CIII

5.5mg of testosterone per actuation*

*Each actuation delivers 0.122 g of gel.
Multi-dose pump capable of
dispensing 60 metered pump
actuations.

For intranasal use only.

Warning: This package is not
child resistant. Keep out of
reach of children.

Total Contents: 11 g / dispenser.

Marketed by:
Acerus Pharmaceuticals Corporation
Toronto, Ontario, M4W 3E2, Canada

ACERUS
PHARMA

Manufactured by:
Haupt Pharma Amareg GmbH
Donaustaufer Str. 378
Regensburg, Bavaria D93055, Germany

Rx ONLY